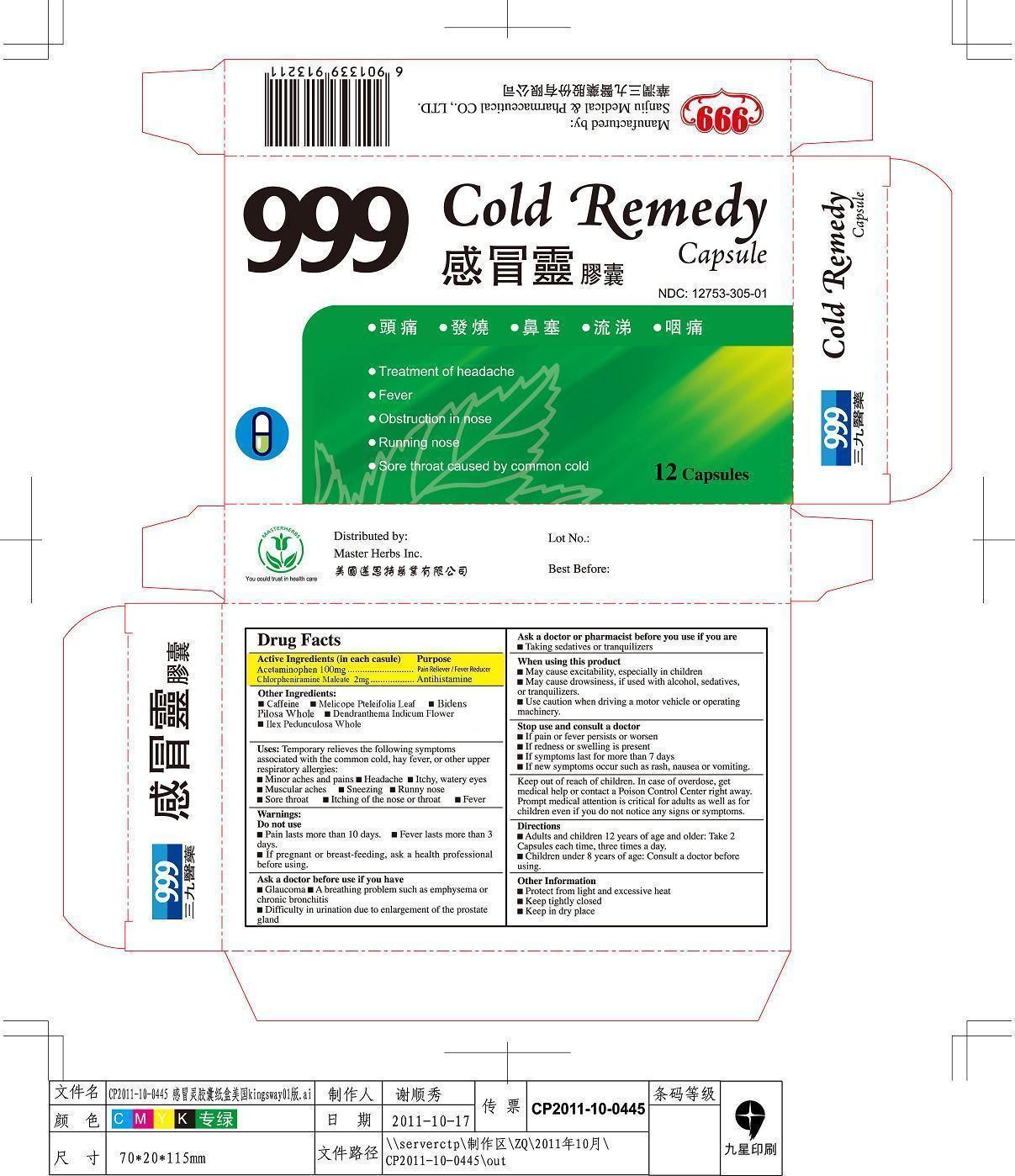 DRUG LABEL: 999 COLD REMEDY
NDC: 12753-305 | Form: CAPSULE
Manufacturer: China Resources Sanjiu Medical & Pharmaceutical Co Ltd
Category: otc | Type: HUMAN OTC DRUG LABEL
Date: 20130917

ACTIVE INGREDIENTS: Acetaminophen 100 mg/6000 mg; CHLORPHENIRAMINE MALEATE 2 mg/6000 mg
INACTIVE INGREDIENTS: CAFFEINE; MELICOPE PTELEIFOLIA LEAF; Bidens Pilosa Whole; Dendranthema indicum flower; ilex Pedunculosa whole

999 COLD REMEDY CAPSULE

Active Ingredients

Acetaminophen 100 mg

Chlorpheniramine Maleate 2 mg

Purpose

Acetaminophen Pain Reliever/Fever Reducer

Chlorpheniramine Maleate Antihistamine

Use

Uses: Temporarily relieves the following symptoms associated with the common cold, hay fever, or other upper resporatory allergies

Minor aches and pains

Headache

Itchy, watery eyes

Muscular aches

Sneezing

Runny nose

Sore Throat

Itching of the nose or throat

Fever

Warnings

Do not use if

Pain lasts more than 10 days.

Fever lasts more than 3 days

Ask a doctor before use if you have

Glaucoma

A breathing problem such as emphysema or chronic bronchitis

Difficulty in urination due to enlargement of the prostate gland

Ask a doctor or pharmacist before you use if you are

Taking sedatives or transquilizers

When using this product

May cause excitability, especially in children

May cause drowsiness, if used with alcohol, sedatives, or transquilizers.

Use caution when driving a motor vehicle or operating machinery.

Stop use and consult a doctor

If pain or fever persisits or worsen

If redness or swelling is present

If symptoms last for more than 7 days

If new symptoms occur such as rash, nausea or vomitting.

Warnings

If preganent or breast-feeding, ask a health professional before using.

Stop use and consult a doctor

Keep out of reach of children. In case of overdose, get medical help or contact a Poison Control Center right away. Prompt medical attention is critical for adults as well as for children even if you do not notice any signs or symptoms.

Directions

Adults and children 12 years of age and older: Take 2 capsules each time, three times a day.

Children under 8 years of age: Consult a doctor before using.

Other Information

Protect from light and excessive heat

Keep tightly closed

Keep in dry place

Other Ingredients

Cafferine

Melicope Pteleiforlia Leaf

Bidens Pilosa Whole

Dendranthema Indicum Flower

Ilex Pedunculosa Whole